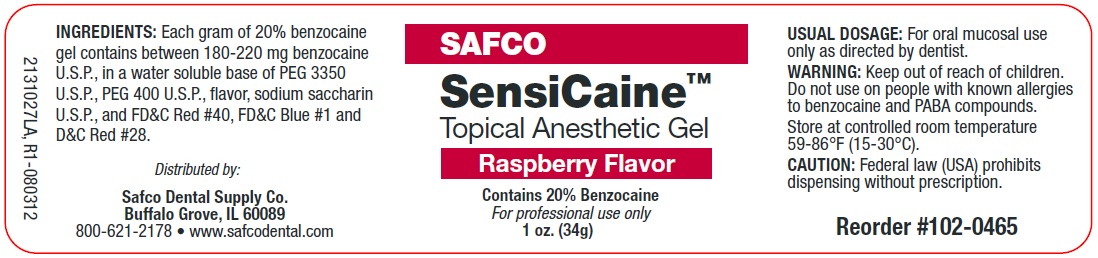 DRUG LABEL: Topical Anesthetic 
                  
NDC: 67239-0208 | Form: GEL
Manufacturer: Safco Dental Supply Co.
Category: otc | Type: HUMAN OTC DRUG LABEL
Date: 20171217

ACTIVE INGREDIENTS: Benzocaine 200 mg/1 g
INACTIVE INGREDIENTS: Polyethylene Glycol 400; Saccharin Sodium; Polyethylene Glycol 3350; Water; FD&C RED NO. 40; FD&C BLUE NO. 1; D&C RED NO. 28

SensiCaine Topical Anesthetic Gel Raspberry Flavor

ACTIVE INGREDIENT

INGREDIENTS

Each gram of 20% benzocaine gel contains between 180-220 mg benzocaine U.S.P., in a water soluble base of PEG 3350 U.S.P., PEG 400 U.S.P., flavor, sodium saccharin U.S.P., and FD&C Red #40, FD&C Blue #1 and D&C Red #28.

USUAL DOSAGE

For oral mucosal use only as directed by a dentist.

WARNING

Keep out of reach of children. Do not use on people with known allergies to benzocaine and PABA compounds.

HOW SUPPLIED

STORAGE AND HANDLING

Store at controlled room temperature 59-86°F (15-30°C).

INDICATIONS AND USAGE

CAUTION

Federal law prohibits dispensing without a prescription.

Distributed by:
Safco Dental Supply Co.
Buffalo Grove, IL 60089
800-621-2178
www.safcodental.com

PRINCIPAL DISPLAY PANEL - Jar Label

SAFCO
SensiCaine

Topical Anesthetic Gel

Raspberry Flavor

Contains 20% Benzocaine

For Professional Use Only

1 oz. (34 g)